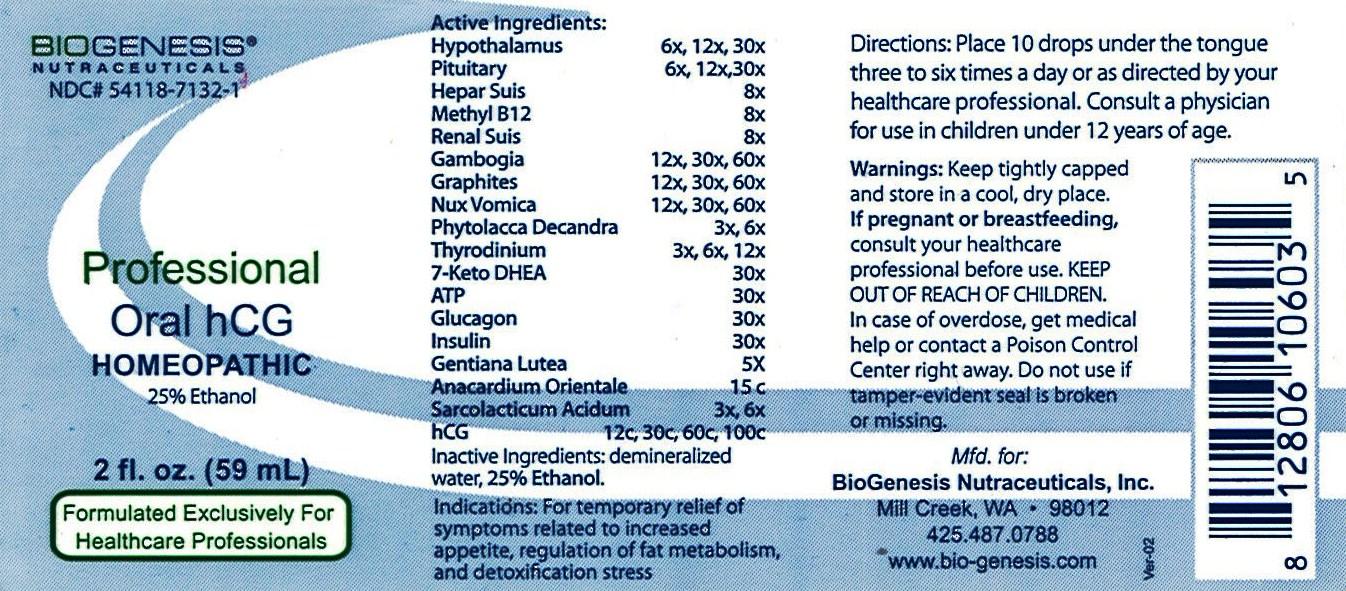 DRUG LABEL: Oral HCG Homeopathic
NDC: 54118-7132 | Form: SOLUTION/ DROPS
Manufacturer: ABCO Laboratories, Inc.
Category: homeopathic | Type: HUMAN OTC DRUG LABEL
Date: 20140305

ACTIVE INGREDIENTS: BOS TAURUS HYPOTHALAMUS 6 [hp_X]/59 mL; BOS TAURUS PITUITARY GLAND 6 [hp_X]/59 mL; PORK LIVER 8 [hp_X]/59 mL; METHYLCOBALAMIN 8 [hp_X]/59 mL; PORK KIDNEY 8 [hp_X]/59 mL; GAMBOGE 12 [hp_X]/59 mL; GRAPHITE 12 [hp_X]/59 mL; STRYCHNOS NUX-VOMICA SEED 12 [hp_X]/59 mL; PHYTOLACCA AMERICANA ROOT 3 [hp_X]/59 mL; 7-KETO-DEHYDROEPIANDROSTERONE 30 [hp_X]/59 mL; ADENOSINE TRIPHOSPHATE 30 [hp_X]/59 mL; GLUCAGON 30 [hp_X]/59 mL; INSULIN HUMAN 30 [hp_X]/59 mL; GENTIANA LUTEA ROOT 5 [hp_X]/59 mL; SEMECARPUS ANACARDIUM JUICE 15 [hp_C]/59 mL; LACTIC ACID, L- 3 [hp_X]/59 mL; GONADOTROPHIN, CHORIONIC 12 [hp_C]/59 mL
INACTIVE INGREDIENTS: WATER; ALCOHOL

Oral HCG Homeopathic

ACTIVE INGREDIENT

- Hypothalamus 6x, 12x, 30x
- Pituitary 6x, 12x, 30x
- Hepar Suis 8x
- Methyl B12 8x
- Renal Suis 8x
- Gambogia 12x, 30x, 60x
- Graphites 12x, 30x, 60x
- Nux Vomica 12x, 30x, 60x
- Phytolacca Decandra 3x, 6x
- 7-Keto DHEA 30x
- ATP 30x
- Glucagon 30x
- Insulin 30x
- Gentiana Lutea 5x
- Anacardium Orientale 15c
- Sarcolacticum Acidum 3x, 6x
- HCG 12c,30c, 60c, 100c

PURPOSE

- Indications: For temporary relief of symptoms related to increased appetite, regulation of fat metabolism, and detoxification stress

- Keep out of reach of children

INDICATIONS AND USAGE

- Place 10 drops under the tongue three to six times a day
- or as directed by your healthcare professional
- Consult a physician for use in children under 12 years of age

WARNINGS

- Keep tightly capped and store in a cool, dry place
- If pregnant or breastfeeding, consult your healthcare professional before use
- Keep out of reach of children
- In case of overdose, get medical help or contact a Poison Control Center right away
- Do not use if either tamper-evident seal is broken or missing

DOSAGE AND ADMINISTRATION

- Place 10 drops under the tongue three to six times a day
- or as directed by your healthcare professional
- Consult a physician for use in children under 12 years of age

INACTIVE INGREDIENT

- Demineralized water
- 12% ethanol

- image of label
- oralhcg.jpg